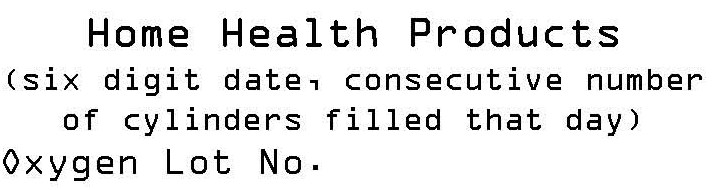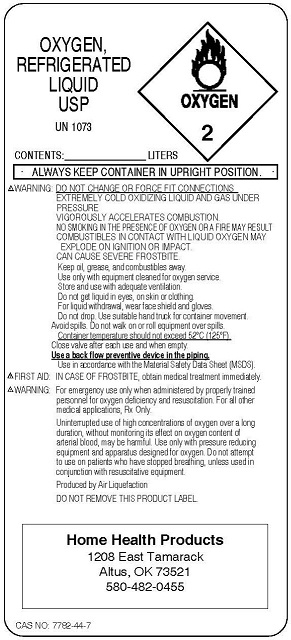 DRUG LABEL: Oxygen
NDC: 66222-0001 | Form: GAS
Manufacturer: JCMH Home Health Products
Category: prescription | Type: HUMAN PRESCRIPTION DRUG LABEL
Date: 20091204

ACTIVE INGREDIENTS: Oxygen 99 L/100 L

Oxygen